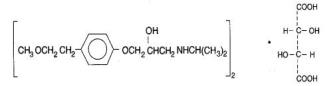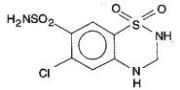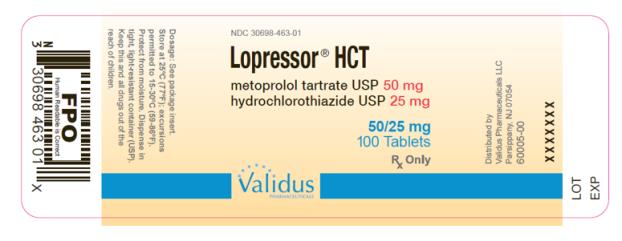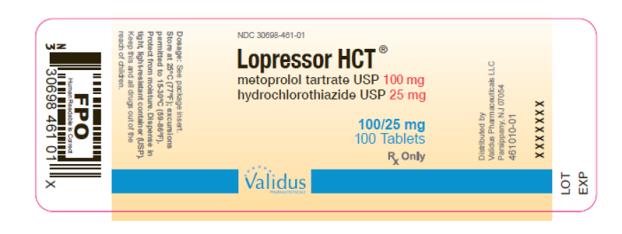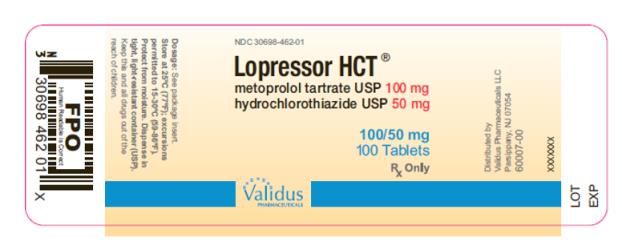 DRUG LABEL: Lopressor HCT
NDC: 30698-463 | Form: TABLET
Manufacturer: Validus Pharmaceuticals LLC
Category: prescription | Type: HUMAN PRESCRIPTION DRUG LABEL
Date: 20230913

ACTIVE INGREDIENTS: METOPROLOL TARTRATE 50 mg/1 1; HYDROCHLOROTHIAZIDE 25 mg/1 1
INACTIVE INGREDIENTS: CELLULOSE, MICROCRYSTALLINE; SILICON DIOXIDE; SODIUM STARCH GLYCOLATE TYPE A POTATO; FD&C BLUE NO. 1; MAGNESIUM STEARATE; LACTOSE, UNSPECIFIED FORM; POLYETHYLENE GLYCOL, UNSPECIFIED; PROPYLENE GLYCOL; POVIDONE; STARCH, CORN; STEARIC ACID; SUCROSE

HIGHLIGHTS OF PRESCRIBING INFORMATION

These highlights do not include all the information needed to use LOPRESSOR HCT safely and effectively. See full prescribing information for LOPRESSOR HCT
LOPRESSOR HCT (metoprolol tartrate and hydrochlorothiazide) tablets, for oral use
Initial U.S. Approval: 1984

1 INDICATIONS AND USAGE

LOPRESSOR HCT is the combination tablet of metoprolol tartrate, a beta adrenoceptor blocker and hydrochlorothiazide (HCTZ), a thiazide diuretic, indicated for the treatment of hypertension, to lower blood pressure. Lowering blood pressure reduces the risk of fatal and nonfatal cardiovascular events, primarily strokes and myocardial infarctions. (1)

2 DOSAGE AND ADMINISTRATION

- Usual dose range: Hydrochlorothiazide 12.5 to 25 mg and metoprolol tartrate 100 mg dosed once daily. (2.1)

3 DOSAGE FORMS AND STRENGTHS

Tablets (metoprolol tartrate/hydrochlorothiazide: 50/25mg; 100/25mg; 100/50mg (3)

4 CONTRAINDICATIONS

- Hypersensitivity to metoprolol tartrate or hydrochlorothiazide or other sulfonamide-derived drugs. (4)
- Cardiogenic shock or decompensated heart failure. (4)
- Sinus bradycardia, sick sinus syndrome, and greater than first-degree block unless a permanent pacemaker is in place. (4)
- Anuria. (4)

5 WARNINGS AND PRECAUTIONS

- Abrupt cessation may exacerbate myocardial ischemia. (5.1)
- May worsen congestive heart failure. (5.2)
- Bronchospasm: Avoid beta-blockers. (5.3)
- Bradycardia. (5.4)
- Avoid discontinuing therapy prior to major surgery. (5.5)
- Diabetes: May mask symptoms of hypoglycemia and alter glucose levels; monitor. (5.6)
- Monitor serum electrolytes and creatinine periodically. (5.7)
- Peripheral vascular disease: Can aggravate symptoms of arterial insufficiency. (5.9)
- Pheochromocytoma: First initiate therapy with an alpha blocker. (5.10)
- Abrupt withdrawal in thyrotoxicosis might precipitate a thyroid storm. (5.11)
- Patients may be unresponsive to the usual doses of epinephrine used to treat allergic reaction. (5.12)

6 ADVERSE REACTIONS

To report SUSPECTED ADVERSE REACTIONS, contact Validus Pharmaceuticals LLC at 1-866-982-5438 or FDA at 1-800-FDA-1088 or www.fda.gov/medwatch.

7 DRUG INTERACTIONS

- Catecholamine-depleting drugs (e.g., MAO inhibitors): Hypotension, bradycardia. (7.1)
- CYP2D6 inhibitors: Increased metoprolol concentration. (12.3)
- Digitalis glycosides, clonidine, diltiazem and verapamil: Bradycardia. (5.4, 7.1)
- Clonidine: Rebound hypertension following clonidine withdrawal. (7.1)

- Antidiabetic drugs: Dosage adjustment may be required. (7.2)
- Cholestyramine and colestipol: Reduced absorption of thiazides. (7.2)
- Lithium: Risk of lithium toxicity. (7.2)
- Non-Steroidal Anti-Inflammatory Drugs (NSAIDs): Reduced diuretic, natriuretic, and antihypertensive effects of diuretics. (7.2)

FULL PRESCRIBING INFORMATION

1 INDICATIONS AND USAGE

LOPRESSOR HCT is indicated for the treatment of hypertension, to lower blood pressure. Lowering blood pressure lowers the risk of fatal and non-fatal cardiovascular events, primarily strokes and myocardial infarctions. These benefits have been seen in controlled trials of antihypertensive drugs from a wide variety of pharmacologic classes including metoprolol.

Control of high blood pressure should be part of comprehensive cardiovascular risk management, including, as appropriate, lipid control, diabetes management, antithrombotic therapy, smoking cessation, exercise, and limited sodium intake. Many patients will require more than 1 drug to achieve blood pressure goals. For specific advice on goals and management, see published guidelines, such as those of the National High Blood Pressure Education Program’s Joint National Committee on Prevention, Detection, Evaluation, and Treatment of High Blood Pressure (JNC).

Numerous antihypertensive drugs, from a variety of pharmacologic classes and with different mechanisms of action, have been shown in randomized controlled trials to reduce cardiovascular morbidity and mortality, and it can be concluded that it is blood pressure reduction, and not some other pharmacologic property of the drugs, that is largely responsible for those benefits. The largest and most consistent cardiovascular outcome benefit has been a reduction in the risk of stroke, but reductions in myocardial infarction and cardiovascular mortality also have been seen regularly.

Elevated systolic or diastolic pressure causes increased cardiovascular risk, and the absolute risk increase per mmHg is greater at higher blood pressures, so that even modest reductions of severe hypertension can provide substantial benefit. Relative risk reduction from blood pressure reduction is similar across populations with varying absolute risk, so the absolute benefit is greater in patients who are at higher risk independent of their hypertension (for example, patients with diabetes or hyperlipidemia), and such patients would be expected to benefit from more aggressive treatment to a lower blood pressure goal.

Some antihypertensive drugs have smaller blood pressure effects (as monotherapy) in black patients, and many antihypertensive drugs have additional approved indications and effects (e.g., on angina, heart failure, or diabetic kidney disease). These considerations may guide selection of therapy.

LOPRESSOR HCT may be administered with other antihypertensive agents.

Limitation of Use

LOPRESSOR HCT is not indicated for initial therapy of hypertension. If the fixed combination represents the dose titrated to the individual patient’s needs, therapy with the fixed combination may be more convenient than with the separate components.

2 DOSAGE AND ADMINISTRATION

2.1 Recommended Dosage

Titrate doses of individual components before switching to LOPRESSOR HCT.

Administer LOPRESSOR HCT with or immediately following meals.

Hydrochlorothiazide is usually given at a dosage of 12.5 mg to 50 mg per day. The usual initial dosage of metoprolol is 100 mg daily in single or divided doses. Dosage may be increased gradually until optimum blood pressure control is achieved.

Once daily dosing may not maintain the full effect for the entire dosing period, particularly at lower doses. In such patients, consider administration in divided doses.

Dosing regimens that exceed 50 mg of hydrochlorothiazide per day are not recommended.

3 DOSAGE FORMS AND STRENGTHS

LOPRESSOR HCT (metoprolol tartrate and hydrochlorothiazide) is supplied as capsule-shaped tablets in the following strengths:

50 mg / 25 mg: white and mottled-blue, scored (imprinted LOPHCT on one side and 463 twice on the scored side)

100 mg / 25 mg: white and mottled-pink, scored (imprinted LOPHCT on one side and 461 twice on the scored side)

100 mg / 50 mg: white and mottled-yellow, scored (imprinted LOPHCT on one side and 462 twice on the scored side)

4 CONTRAINDICATIONS

LOPRESSOR HCT is contraindicated in patients with:

- Cardiogenic shock or decompensated heart failure.
- Sinus bradycardia, sick sinus syndrome, and greater than first-degree block unless a permanent pacemaker is in place.
- Anuria
- Hypersensitivity to metoprolol tartrate or hydrochlorothiazide or to other sulfonamide-derived drugs.

5 WARNINGS AND PRECAUTIONS

5.1 Abrupt Cessation of Therapy

Following abrupt cessation of therapy with beta adrenergic blockers, exacerbations of angina pectoris and myocardial infarction may occur. When discontinuing chronically administered LOPRESSOR HCT, particularly in patients with ischemic heart disease, gradually reduce the dosage over a period of 1 to 2 weeks and monitor the patient. If angina markedly worsens or acute coronary ischemia develops, promptly resume therapy and take measures appropriate for the management of unstable angina. Warn patients not to interrupt therapy without their physician’s advice. Because coronary artery disease is common and may be unrecognized, avoid abruptly discontinuing metoprolol tartrate in patients treated only for hypertension.

5.2 Heart Failure

Worsening cardiac failure may occur during up-titration of beta-blockers. If such symptoms occur, increase diuretics and restore clinical stability before advancing the dose of metoprolol. It may be necessary to lower the dose of metoprolol tartrate or temporarily discontinue it. Such episodes do not preclude subsequent successful titration of metoprolol tartrate.

5.3 Bronchospastic Disease

Beta adrenergic blockers can cause bronchospasm. Patients with bronchospastic diseases should, in general, not receive beta-blockers. Because of its relative beta1 cardio-selectivity, however, metoprolol tartrate may be used in patients with bronchospastic disease who do not respond to, or cannot tolerate, other antihypertensive treatment. Because beta1-selectivity is not absolute, use the lowest possible dose of metoprolol tartrate and have bronchodilators (e.g., beta2-agonists) readily available or administered concomitantly.

5.4 Bradycardia

Bradycardia, including sinus pause, heart block, and cardiac arrest have occurred with the use of LOPRESSOR HCT. Patients with first-degree atrioventricular block, sinus node dysfunction, conduction disorders (including Wolff-Parkinson-White) or on concomitant drugs [see Drug Interactions (7)] that cause bradycardia may be at increased risk. Monitor heart rate in patients receiving LOPRESSOR HCT. If severe bradycardia develops, reduce or stop LOPRESSOR HCT.

5.5 Major Surgery

Avoid initiation of high-dose regimen of LOPRESSOR HCT in patients with cardiovascular risk factors undergoing non-cardiac surgery, since use in such patients has been associated with bradycardia, hypotension, stroke and death.

Chronically administered beta-adrenergic blockers should not be routinely withdrawn prior to major surgery; however, the impaired ability of the heart to respond to reflex adrenergic stimuli may augment the risks of general anesthesia and surgical procedures [see Warnings and Precautions (5.1)].

5.6 Masked Symptoms of Hypoglycemia

Beta-blockers may prevent early warning signs of hypoglycemia, such as tachycardia, and increase the risk for severe or prolonged hypoglycemia at anytime during treatment, especially in patients with diabetes mellitus or children and patients who are fasting (i.e., surgery, not eating regularly, or are vomiting). If severe hypoglycemia occurs, patients should be instructed to seek emergency treatment.

5.7 Electrolyte and Metabolic Effects

LOPRESSOR HCT contains hydrochlorothiazide which can cause hypokalemia and hyponatremia. Hypomagnesemia can result in hypokalemia which may be difficult to treat despite potassium repletion. Monitor serum electrolytes periodically.

Hydrochlorothiazide may alter glucose tolerance and raise serum levels of cholesterol and triglycerides.

Hydrochlorothiazide reduces clearance of uric acid and may cause or exacerbate hyperuricemia and precipitate gout in susceptible patients.

Hydrochlorothiazide decreases urinary calcium excretion and may cause elevations of serum calcium. Monitor calcium levels.

5.8 Renal Impairment

Patients with chronic kidney disease, severe heart failure, or volume depletion may be at increased risk for developing acute renal failure on drugs containing hydrochlorothiazide, including LOPRESSOR HCT.

5.9 Peripheral Vascular Disease

Beta-blockers can precipitate or aggravate symptoms of arterial insufficiency in patients with peripheral vascular disease.

5.10 Pheochromocytoma

If LOPRESSOR HCT is used in the setting of pheochromocytoma, it should be given in combination with an alpha blocker, and only after the alpha blocker has been initiated. Administration of beta-blockers alone in the setting of pheochromocytoma has been associated with a paradoxical increase in blood pressure due to the attenuation of beta-mediated vasodilatation in skeletal muscle.

5.11 Thyrotoxicosis

Beta-adrenergic blockade may mask certain clinical signs of hyperthyroidism, such as tachycardia. Abrupt withdrawal of beta-blockade may precipitate a thyroid storm.

5.12 Anaphylactic Reaction

While taking beta-blockers, patients with a history of severe anaphylactic reactions to a variety of allergens may be more reactive to repeated challenge and may be unresponsive to the usual doses of epinephrine used to treat an allergic reaction.

5.13 Acute Myopia and Second Angle-Closure Glaucoma

Hydrochlorothiazide, a sulfonamide, can cause acute transient myopia and acute angle-closure glaucoma (idiosyncratic reactions). Symptoms include acute onset of decreased visual acuity or ocular pain and typically occur within hours to weeks of hydrochlorothiazide initiation. Risk factors for developing acute angle-closure glaucoma may include a history of sulfonamide or penicillin allergy.

Untreated acute angle-closure glaucoma can lead to permanent vision loss. Given that LOPRESSOR HCT contains hydrochlorothiazide, if these symptoms occur, discontinue LOPRESSOR HCT. Consider prompt medical or surgical treatment if the intraocular pressure remains uncontrolled.

5.14 Exacerbation of Systemic Lupus Erythematosus

Hydrochlorothiazide can exacerbate or activate systemic lupus erythematosus.

6 ADVERSE REACTIONS

The following adverse reactions are described in more detail elsewhere in the label;

- Worsening angina or myocardial infarction [see Warnings and Precautions (5)]
- Worsening heart failure [see Warnings and Precautions (5)]
- Worsening AV block [see Contraindications (4)]

6.2 Post-Marketing Experience

The following adverse reactions have been reported in postmarketing experience: adverse reactions have been identified during post approval use of LOPRESSOR HCT. Because these reactions are reported voluntarily from a population of uncertain size, it is not always possible to reliably estimate their frequency or establish a causal relationship to drug exposure.

Metoprolol

Confusional state, an increase in blood triglycerides and a decrease in High Density Lipoprotein (HDL). Very rare reports of hepatitis, jaundice and non-specific hepatic dysfunction. Isolated cases of transaminase, alkaline phosphatase, and lactic dehydrogenase elevations have also been reported.

Hydrochlorothiazide

Digestive: Pancreatitis, jaundice (intrahepatic cholestatic), sialadenitis, vomiting, diarrhea, cramping, nausea, gastric irritation, constipation, anorexia.

Cardiovascular: Orthostatic hypotension (may be potentiated by alcohol, barbiturates, or narcotics).

Neurologic: Vertigo, dizziness, transient blurred vision, headache, paresthesia, xanthopsia, weakness, restlessness.

Musculoskeletal: Muscle spasm.

Hematologic: Aplastic anemia, agranulocytosis, leukopenia, thrombocytopenia.

Metabolic: Hyperglycemia, glycosuria, hyperuricemia.

Hypersensitive Reactions: Necrotizing angiitis, Stevens-Johnson syndrome, respiratory distress including pneumonitis and pulmonary edema, purpura, urticaria, rash, photosensitivity.

Other beta-adrenergic agent reactions

A variety of adverse reactions have been reported with other beta-adrenergic blocking agents and should be considered potential adverse reactions to Lopressor.

Central Nervous System: Reversible mental depression progressing to catatonia; visual disturbances; hallucinations; an acute reversible syndrome characterized by disorientation for time and place, emotional lability, clouded sensorium, and decreased performance on neuropsychometrics.

Hematologic: Agranulocytosis, nonthrombocytopenic purpura, thrombocytopenic purpura.

Hypersensitive Reactions: Laryngospasm and respiratory distress.

7 DRUG INTERACTIONS

7.1 Drug Interactions with Metoprolol

Catecholamine Depleting Drugs:

The concomitant use of catecholamine-depleting drugs (e.g., reserpine, monoamine oxidase (MAO) inhibitors) with beta adrenergic blockers may have an additive affect and increase the risk of hypotension or bradycardia.

CYP2D6 Inhibitors:

Drugs that are strong inhibitors of CYP2D6 such as quinidine, fluoxetine, paroxetine, and propafenone were shown to double metoprolol concentrations. While there is no information about moderate or weak inhibitors, these too are likely to increase metoprolol concentration. Increases in plasma concentration decrease the cardioselectivity of metoprolol [see Clinical Pharmacology (12.3)]. Monitor patients closely when the combination cannot be avoided.

Digitalis, Clonidine, and Calcium Channel Blockers:

Digitalis glycosides, clonidine, diltiazem and verapamil slow atrioventricular conduction and decrease heart rate. Concomitant use with beta blockers can increase the risk of bradycardia.

If clonidine and a beta blocker, such as metoprolol are coadministered, withdraw the beta-blocker several days before the gradual withdrawal of clonidine because beta-blockers may exacerbate the rebound hypertension that can follow the withdrawal of clonidine. If replacing clonidine by beta-blocker therapy, delay the introduction of beta-blockers for several days after clonidine administration has stopped.

7.2 Drug Interactions with Hydrochlorothiazide

Antidiabetic drugs (oral agents and insulin): Dosage adjustment of the antidiabetic drug may be required.

Ion exchange resins: Absorption of hydrochlorothiazide is impaired in the presence of anionic exchange resins. Single doses of either cholestyramine or colestipol resins bind the hydrochlorothiazide and reduce its absorption from the gastrointestinal tract by up to 85% and 43%, respectively. Stagger the dosage of hydrochlorothiazide and ion exchange resins (e.g., cholestyramine and colestipol resins) such that hydrochlorothiazide is administered at least 4 hours before or 4-6 hours after the administration of resins to minimize the interaction.

Lithium: Diuretics reduce the renal clearance of lithium and increase the risk of lithium toxicity. Monitor serum lithium concentrations during concurrent use.

Non-Steroidal Anti-Inflammatory Drugs: NSAIDs can reduce the diuretic, natriuretic, and antihypertensive effects of thiazide diuretics.

8 SPECIFIC POPULATIONS

8.1 Pregnancy

Risk Summary

Untreated hypertension during pregnancy can lead to adverse outcomes for the mother and the fetus (see Clinical Considerations). Available data from published observational studies have not demonstrated a drug-associated risk of major birth defects, miscarriage, or adverse maternal or fetal outcomes with metoprolol use during pregnancy. However, there are inconsistent reports of intrauterine growth restriction, preterm birth, and perinatal mortality with maternal use of beta blockers, including metoprolol, during pregnancy (see Data). There have been rare reports of jaundice, thrombocytopenia, and electrolyte imbalances in infants exposed to thiazide medications during pregnancy.

In animal reproduction studies, metoprolol has been shown to increase post-implantation loss and decrease neonatal survival in rats at oral dosages up to 24 times, on a mg/m^2 basis, the daily dose of 200 mg in a 60-kg patient. The combination of metoprolol tartrate/hydrochlorothiazide administered to rats from mid-late gestation through lactation also produced increased post-implantation loss and decreased neonatal survival (see Data).

The estimated background risk of major birth defects and miscarriage for the indicated population is unknown. All pregnancies have a background risk of birth defect, loss, or other adverse outcomes. In the U.S. general population, the estimated background risk of major birth defects and miscarriage in clinically recognized pregnancies is 2 to 4% and 15 to 20%, respectively.

Clinical consideration

Disease-associated maternal and/or embryo/fetal risk

Hypertension in pregnancy increases the maternal risk for pre-eclampsia, gestational diabetes, premature delivery, and delivery complications (e.g., need for cesarean section, and post-partum hemorrhage). Hypertension increases the fetal risk for intrauterine growth restriction and intrauterine death. Pregnant women with hypertension should be carefully monitored and managed accordingly.

Fetal/Neonatal adverse reactions

Metoprolol

Metoprolol crosses the placenta. Neonates born to mothers who are receiving metoprolol during pregnancy, may be at risk for hypotension, hypoglycemia, bradycardia, and respiratory depression. Observe neonates for symptoms of hypotension, bradycardia, hypoglycemia and respiratory depression and manage accordingly.

Data

Human Data

Data from published observational studies did not demonstrate an association of major congenital malformations and use of either metoprolol or hydrochlorothiazide in pregnancy. The published literature has reported inconsistent findings of intrauterine growth retardation, preterm birth and perinatal mortality with maternal use of metoprolol during pregnancy; however, these studies have methodological limitations hindering interpretation. Methodological limitations include retrospective design, concomitant use of other medications, and other unadjusted confounders that may account for the study findings including the underlying disease in the mother. These observational studies cannot definitely establish or exclude any drug-associated risk during pregnancy.

Animal Data

Oral administration of metoprolol tartrate/hydrochlorothiazide combinations to pregnant rats during organogenesis at doses up to 200/50 mg/kg/day (10 and 20 times the MRHD on a mg/m^2 basis for metoprolol and hydrochlorothiazide, respectively) or to pregnant rabbits at doses up to 25/6.25 mg/kg/day (about 2.5 and 5 times the MRHD on a mg/m^2 basis for metoprolol and hydrochlorothiazide, respectively) produced no teratogenic effects. A 200/50 mg/kg/day metoprolol tartrate/hydrochlorothiazide combination administered to rats from mid-late gestation through lactation produced increased post-implantation loss and decreased neonatal survival.

Metoprolol

Metoprolol has been shown to increase post-implantation loss and decrease neonatal survival in rats at doses up to 24 times, on a mg/m^2 basis, the daily dose of 200 mg in a 60-kg patient. Distribution studies in mice confirm exposure of the fetus when metoprolol tartrate is administered to the pregnant animal. These studies have revealed no evidence of impaired fertility or teratogenicity.

Hydrochlorothiazide

Hydrochlorothiazide administered to pregnant mice and rats during organogenesis at doses up to 3000 and 1000 mg/kg/day (600 and 400 times the MRHD on a mg/m^2 basis), respectively, produced no harm to the fetus. Thiazides cross the placental barrier and appear in the cord blood.

8.2 Lactation

Risk Summary

There are no data on the presence of LOPRESSOR HCT in human milk, the effects on the breastfed infant, or the effects on milk production. However, data are available on the individual components of LOPRESSOR HCT. Available data from published literature on metoprolol and hydrochlorothiazide report that each drug is present in human milk (see Data). There are no reports of adverse effects on breastfed infants exposed to metoprolol or hydrochlorothiazide during lactation. Doses of hydrochlorothiazide associated with clinically significant diuresis have been associated with impaired milk production. There is no information regarding the effects of metoprolol on milk production. Monitor infants exposed to LOPRESSOR HCT though breastmilk for drowsiness or poor feeding (see Clinical Considerations).

The developmental and health benefits of breastfeeding should be considered along with the mother’s clinical need for LOPRESSOR HCT and any potential adverse effects on the breastfed child from LOPRESSOR HCT or from the underlying maternal condition.

Clinical Considerations

Monitor the breastfed infant for bradycardia or somnolence.

Data

Metoprolol

Based on published case reports, the estimated daily infant dose of metoprolol received from breastmilk ranged from 0.05 mg to less than 1 mg. The estimated relative infant dosage was 0.5% to 2% of the mother’s weight-adjusted dosage.

In two women who were taking unspecified amount of metoprolol, milk samples were taken after one dose of metoprolol. The estimated amount of metoprolol and alpha-hydroxymetoprolol in breast milk is reported to be less than 2% of the mother's weight-adjusted dosage.

In a small study, breast milk was collected every 2 to 3 hours over one dosage interval, in three mothers (at least 3 months postpartum) who took metoprolol of unspecified amount. The average amount of metoprolol present in breast milk was 71.5 mcg/day (range 17.0 to 158.7). The average relative infant dosage was 0.5% of the mother's weight-adjusted dosage.

Hydrochlorothiazide

A single study involving one woman and her infant showed a peak concentration of 275 mcg/L at 3 hours following 50 mg dose. No drug was detected (< 20 mcg/L) in the infant’s plasma at 2- and 11-hours following mother’s dose.

8.3 Females and Males of Reproductive Potential

Infertility

Males

Based on the published literature, beta blockers (including metoprolol) may cause erectile dysfunction and inhibit sperm motility. No evidence of impaired fertility due to metoprolol or hydrochlorothiazide was observed in rats [see Nonclinical Toxicology (13.1)].

8.4 Pediatric Use

Safety and effectiveness in pediatric patients have not been established.

8.5 Geriatric Use

Clinical studies of Lopressor HCT did not include sufficient numbers of subjects aged 65 and over to determine whether they respond differently from younger subjects. Other reported clinical experience has not identified differences in responses between the elderly and younger patients. Hydrochlorothiazide is known to be substantially excreted by the kidney, and the risk of toxic reactions to this drug may be greater in patients with impaired renal function. Because elderly patients are more likely to have decreased renal function, care should be taken in dose selection, and it may be useful to monitor renal function [see Warnings and Precautions (5.8)]. In general, dose selection for an elderly patient should be cautious, usually starting at the low end of the dosing range, reflecting the greater frequency of decreased hepatic, renal, or cardiac function, and concomitant disease or other drug therapy.

10 OVERDOSAGE

10.1 Signs and Symptoms

The most frequently observed signs expected with overdosage of a beta-adrenergic blocker are bradycardia and bradyarrhythmia, hypotension, heart failure, cardiac conduction disturbances and bronchospasm, atrioventricular block, hypoxia, impairment of consciousness/coma, cardiogenic shock, nausea and vomiting.

With thiazide diuretics, acute intoxication is rare. The most prominent feature of overdose is acute loss of fluid, electrolytes and magnesium. Signs and symptoms of overdose may include hypotension, dizziness, muscle cramps, renal impairment or failure, and sedation/ impairment of consciousness. Altered laboratory findings can also occur (e.g., hypokalemia, hypomagnesemia, hyponatremia, hypochloremia, alkalosis, increased BUN).

10.2 Management

Care should be provided at a facility that can provide appropriate supporting measures, monitoring and supervision as treatment is symptomatic and supportive and there is no specific antidote. Limited data suggest that neither metoprolol nor hydrochlorothiazide is dialyzable. If justified, gastric lavage and/or activated charcoal can be administered.

Based on the expected pharmacologic actions and recommendations for other beta-adrenergic blockers and hydrochlorothiazide, the following measures should be considered when clinically warranted.

Hemodialysis is unlikely to make a useful contribution to metoprolol elimination [see Clinical Pharmacology (12.3)].

Bradycardia and conduction disturbances: Use atropine, adrenergic-stimulating drugs or pacemaker.

Hypotension or shock: Treat underlying bradycardia. Consider intravenous expansion, vasopressors, injection of glucagon (if necessary, followed by an intravenous infusion of glucagon), or intravenous administration of adrenergic drugs such as dobutamine.

Heart failure: Treat bradycardia if present and support hemodynamics with inotropes if necessary.

Bronchospasm: Can usually be reversed by bronchodilators.

11 DESCRIPTION

Lopressor HCT has the antihypertensive effect of Lopressor®, metoprolol tartrate, a beta adrenoreceptor blocker, and hydrochlorothiazide, a thiazide diruetic. It is available as tablets for oral administration. The 50/25 tablets contain 50 mg of metoprolol tartrate USP and 25 mg of hydrochlorothiazide USP; the 100/25 tablets contain 100 mg of metoprolol tartrate USP and 25 mg of hydrochlorothiazide USP; and the 100/50 tablets contain 100 mg of metoprolol tartrate USP and 50 mg of hydrochlorothiazide USP. Metoprolol tartrate USP is (±)-1-(Isopropylamino)-3-[p-(2-methoxyethyl)phenoxy]-2-propanol L-(+)-tartrate (2:1) salt, and its structural formula is

Metoprolol tartrate USP is a white, crystalline powder. It is very soluble in water; freely soluble in methylene chloride, in chloroform, and in alcohol; slightly soluble in acetone; and insoluble in ether. Its molecular weight is 684.82.

Hydrochlorothiazide is 6-chloro-3, 4-dihydro-2 H-1,2,4-benzothiadiazine-7- sulfonamide 1,1-dioxide, and its structural formula is

Hydrochlorothiazide USP is a white, or practically white, practically odorless, crystalline powder. It is freely soluble in sodium hydroxide solution, in n-butylamine, and in dimethylformamide; sparingly soluble in methanol; slightly soluble in water; and insoluble in ether, in chloroform, and in dilute mineral acids. Its molecular weight is 297.73.

Inactive Ingredients: microcrystalline cellulose, colloidal silicon dioxide, D&C Yellow No. 10 (100/50 mg tablets), FD&C Blue No. 1 (50/25 mg tablets), FD&C Red No. 80 and FD&C Yellow No. 6 and FD&C Yellow No. 5 (100/25 mg tablets), lactose monohydrate, magnesium stearate, povidone, sodium starch glycolate, sodium starch glycolate, stearic acid, and Confectioner's Sugar.

12 CLINICAL PHARMACOLOGY

12.1 Mechanism of Action

Metoprolol is a beta1-selective (cardioselective) adrenergic receptor blocker. This preferential effect is not absolute however, and at higher plasma concentrations, metoprolol also inhibits beta2-adrenoreceptors, chiefly located in the bronchial and vascular musculature. Metoprolol has no intrinsic sympathomimetic activity, and membrane-stabilizing activity is detectable only at plasma concentrations much greater than required for beta-blockade. Animal and human experiments indicate that metoprolol slows the sinus rate and decreases AV nodal conduction.

The mechanism of the antihypertensive effects of beta-blocking agents has not been elucidated. However, several possible mechanisms have been proposed: (1) competitive antagonism of catecholamines at peripheral (especially cardiac) adrenergic neuron sites, leading to decreased cardiac output; (2) a central effect leading to reduced sympathetic outflow to the periphery; and (3) suppression of renin activity.

The mechanism of antihypertensive effect of thiazide diuretics is unknown.

12.2 Pharmacodynamics

Metoprolol

Clinical pharmacology studies have confirmed the beta-blocking activity of metoprolol in man, as shown by (1) reduction in heart rate and cardiac output at rest and upon exercise, (2) reduction of systolic blood pressure upon exercise, (3) inhibition of isoproterenol-induced tachycardia, and (4) reduction of reflex orthostatic tachycardia.

Significant beta-blocking effect (as measured by reduction of exercise heart rate) occurs within 1 hour after oral administration, and its duration is dose-related. For example, a 50% reduction of the maximum registered effect after single oral doses of 20, 50, and 100 mg occurred at 3.3, 5.0, and 6.4 hours, respectively, in normal subjects. After repeated oral dosages of 100 mg twice daily, a significant reduction in exercise systolic blood pressure was evident at 12 hours.

There is a linear relationship between the log of plasma levels and reduction of exercise heart rate. However, antihypertensive activity does not appear to be related to plasma levels. Because of variable plasma levels attained with a given dose and lack of a consistent relationship of antihypertensive activity to dose, selection of proper dosage requires individual titration.

The onset of action of thiazides occurs in 2 hours and the peak effect at about 4 hours. The action persists for approximately 6 to 12 hours.

12.3 Pharmacokinetics

Absorption

In man, absorption of metoprolol HCT is rapid and complete. Plasma levels following oral administration, however, approximate 50% of levels following intravenous administration, indicating about 50% first-pass metabolism.

Hydrochlorothiazide is rapidly absorbed, as indicated by peak plasma concentrations 1 to 2.5 hours after oral administration. Plasma levels of the drug are proportional to dose; the concentration in whole blood is 1.6 to 1.8 times higher than in plasma.

Thiazides affect the renal tubular mechanism of electrolyte reabsorption. At maximal therapeutic dosage, all thiazides are approximately equal in their diuretic potency. Thiazides increase excretion of sodium and chloride in approximately equivalent amounts. Natriuresis causes a secondary loss of potassium.

The mechanism of the antihypertensive effect of thiazides is unknown. Thiazides do not affect normal blood pressure.

Effect of Food

Gastrointestinal absorption of hydrochlorothiazide is enhanced when administered with food. Absorption is decreased in patients with congestive heart failure, and the pharmacokinetics are considerably different in these patients.

Distribution

Plasma levels achieved are highly variable after oral administration. Only a small fraction of the drug (about 12%) is bound to human serum albumin. Metoprolol is a racemic mixture of R- and S-enantiomers. Less than 5% of an oral dose of metoprolol is recovered unchanged in the urine; the rest is excreted by the kidneys as metabolites that appear to have no clinical significance. The systemic availability and half-life of metoprolol in patients with renal failure do not differ to a clinically significant degree from those in normal subjects. Consequently, no reduction in dosage is usually needed in patients with chronic renal failure.

Elimination

Thiazides are eliminated rapidly by the kidney. After oral administration of 25 mg to 100 mg doses, 72% to 97% of the dose is excreted in the urine, indicating dose-independent absorption. Hydrochlorothiazide is eliminated from plasma in a biphasic fashion with a terminal half-life of 10 to 17 hours. Plasma protein binding is 67.9%. Plasma clearance is 15.9 to 30.0 L/hr; volume of distribution is 3.6 to 7.8 L/kg.

Specific Populations:

Geriatric Patients

In elderly subjects with clinically normal renal function, there are no significant differences in metoprolol pharmacokinetics compared to young subjects.

Racial or Ethnic Groups

Metoprolol is extensively metabolized by the cytochrome P450 enzyme system in the liver. The oxidative metabolism of metoprolol is under genetic control with a major contribution of the polymorphic cytochrome P450 isoform 2D6 (CYP2D6). There are marked ethnic differences in the prevalence of the poor metabolizers (PM) phenotype. Approximately 7% of Caucasians and less than 1% Asian are poor metabolizers.

12.5 Pharmacogenomics

CYP2D6 is absent in about 8% of Caucasians (poor metabolizers) and about 2% of most other populations. CYP2D6 can be inhibited by several drugs. Poor metabolizers of CYP2D6 will have increased (several-fold) metoprolol blood levels, decreasing metoprolol's cardioselectivity.

13 NONCLINICAL TOXICOLOGY

Lopressor HCT:

Carcinogenicity and mutagenicity studies have not been conducted with Lopressor HCT. Lopressor HCT produced no evidence of impaired fertility in male or female rats administered gavaged doses up to 200/50 mg/kg (about 10 and 20 times the maximum recommended human dose (MRHD) of metoprolol and hydrochlorothiazide, respectively, on a mg/m^2 basis) prior to mating and throughout gestation and rearing of young.

Lopressor:

Long-term studies in animals have been conducted to evaluate carcinogenic potential. In a 2-year study in rats at three oral dosage levels of up to 800 mg/kg per day (41 times, on a mg/m^2 basis, the daily dose of 200 mg for a 60-kg patient), there was no increase in the development of spontaneously occurring benign or malignant neoplasms of any type. The only histologic changes that appeared to be drug related were an increased incidence of generally mild focal accumulation of foamy macrophages in pulmonary alveoli and a slight increase in biliary hyperplasia. In a 21-month study in Swiss albino mice at three oral dosage levels of up to 750 mg/kg per day (about 18 times, on a mg/m^2 basis, the daily dose of 200 mg for a 60-kg patient), benign lung tumors (small adenomas) occurred more frequently in female mice receiving the highest dose than in untreated control animals. There was no increase in malignant or total (benign plus malignant) lung tumors, or in the overall incidence of tumors or malignant tumors. This 21-month study was repeated in CD-1 mice, and no statistically or biologically significant differences were observed between treated and control mice of either sex for any type of tumor.

All mutagenicity tests performed (a dominant lethal study in mice, chromosome studies in somatic cells, a Salmonella/mammalian-microsome mutagenicity test, and a nucleus anomaly test in somatic interphase nuclei) were negative.

No evidence of impaired fertility due to Lopressor was observed in a study performed in rats at doses up to 22 times, on a mg/m^2 basis, the daily dose of 200 mg in a 60 kg patient.

Hydrochlorothiazide:

Two-year feeding studies in mice and rats uncovered no evidence of a carcinogenic potential of hydrochlorothiazide in female mice at doses up to approximately 600 mg/kg/day (about 120 times the MRHD of 25 mg/day on a mg/m^2 basis) or in male and female rats at doses up to approximately 100 mg/kg/day (about 40 times the MRHD on a mg/m^2 basis). However, there was equivocal evidence for hepatocarcinogenicity in male mice.

Hydrochlorothiazide was not genotoxic in the Ames bacterial mutagenicity testor the Chinese Hamster Ovary (CHO) test for chromosomal aberrations. Nor was it genotoxic in vivo assays using mouse germinal cell chromosomes, Chinese hamster bone marrow chromosomes, and the Drosophila sex-linked recessive lethal trait gene. Positive test results were obtained in the in vitro CHO Sister Chromatid Exchange (clastogenicity) and in the Mouse Lymphoma Cell (mutagenicity) assays, and in the Aspergillus nidulans nondisjunction assay at an unspecified concentration.

Hydrochlorothiazide had no adverse effects on the fertility of mice and rats of either sex in studies wherein these species were exposed, via their diet, to doses of up to 100 and 4 mg/kg/day (about 20 and 1.6 times the MRHD, on a mg/m^2 basis), respectively, prior to mating and throughout gestation.

16 HOW SUPPLIED/STORAGE AND HANDLING

Tablets 50/25 - capsule-shaped, white and mottled-blue, scored (imprinted LOPHCT on one side and 463 twice on the scored side), 50 mg of metoprolol tartrate and 25 mg of hydrochlorothiazide

Bottles of 100……………………………………NDC 30698-463- 01

Tablets 100/25 - capsule-shaped, white and mottled-pink, scored (imprinted LOPHCT on one side and 461 twice on the scored side), 100 mg of metoprolol tartrate and 25 mg of hydrochlorothiazide

Bottles of 100……………………………………NDC 30698-461-01

Tablets 100/50 - capsule- shaped, white and mottled-yellow, scored (imprinted LOPHCT on one side and 462 twice on the scored side), 100 mg of metoprolol tartrate and 50 mg of hydrochlorothiazide

Bottles of 100……………………………………NDC 30698-462-01

Store at 77ºF (25ºC); excursions permitted to 59º to 86ºF (15º to 30ºC) [See USP Controlled Room Temperature]. Protect from moisture.

Dispense in a tight, light-resistant container (USP).

17 PATIENT COUNSELING INFORMATION

Inform patients or caregivers that there is a risk of hypoglycemia when Lopressor HCT is given to patients who are fasting or who are vomiting. Instruct patients or caregivers how to monitor for signs of hypoglycemia [see Warnings and Precautions (5.6)].

Advise patients to take Lopressor HCT as directed, with or immediately following meals. If a dose is missed, advise the patient to take only the next scheduled dose (without doubling it). Advise patients to not discontinue Lopressor HCT without consulting their healthcare provider.

Manufactured for and Distributed by:
Validus Pharmaceuticals LLC
Parsippany, NJ 07054
info@validuspharma.com
www.validuspharma.com
1-866-982-5438

© 2023 Validus Pharmaceuticals LLC

60006-05

PRINCIPAL DISPLAY PANEL

NDC 30698-463-01

Lopressor HCT®
metoprolol tartrate USP 50 mg
hydrochlorothiazide USP 25 mg

50/25 mg
100 Tablets

Rx Only

PRINCIPAL DISPLAY PANEL

NDC 30698-461-01

Lopressor HCT®
metoprolol tartrate USP 100 mg
hydrochlorothiazide USP 25 mg

100/25 mg
100 Tablets

Rx Only

PRINCIPAL DISPLAY PANEL

NDC 30698-462-01

Lopressor HCT®
metoprolol tartrate USP 100 mg
hydrochlorothiazide USP 50 mg

100/50 mg
100 Tablets

Rx Only